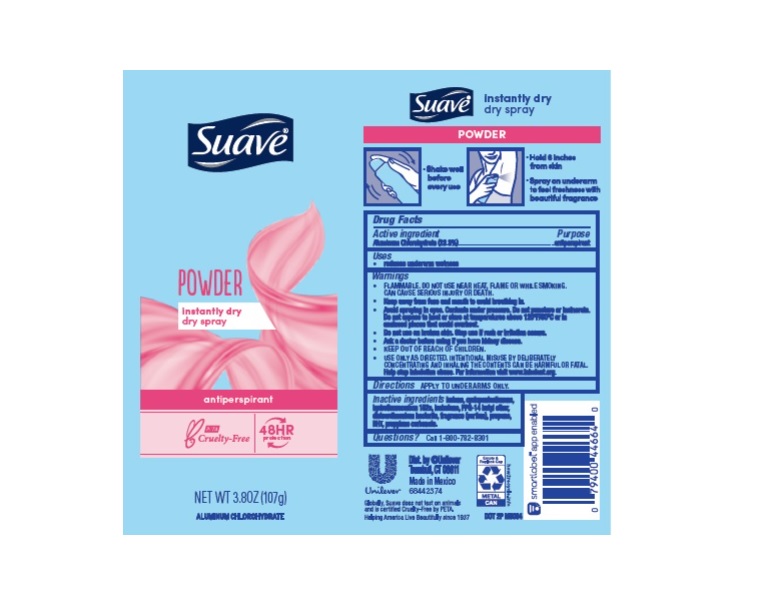 DRUG LABEL: Suave
NDC: 64942-1823 | Form: AEROSOL, SPRAY
Manufacturer: Conopco Inc. d/b/a/ Unilever
Category: otc | Type: HUMAN OTC DRUG LABEL
Date: 20221207

ACTIVE INGREDIENTS: ALUMINUM CHLOROHYDRATE 23.3 g/100 g
INACTIVE INGREDIENTS: BUTANE; CYCLOMETHICONE 5; 1,1-DIFLUOROETHANE; PPG-14 BUTYL ETHER; DISTEARDIMONIUM HECTORITE; BUTYLATED HYDROXYTOLUENE; PROPYLENE CARBONATE; PROPANE; ISOBUTANE

Suave Powder 48HR Protection Dry Spray Antiperspirant

SUAVE POWDER 48HR PROTECTION DRY SPRAY ANTIPERSPIRANT - aluminum chlorohydrate aerosol, spray

Suave Powder 48HR Protection Dry Spray Antiperspirant

Drug Facts

Active ingredient
Aluminum Chlorohydrate (23.3%)

Purpose

antiperspirant

Uses

reduces underarm wetness

Warnings

• FLAMMABLE. DO NOT USE NEAR HEAT, FLAME, OR WHILE SMOKING. CAN CAUSE SERIOUS INJURY OR DEATH
• Keep away from face and mouth to avoid breathing in.
• Avoid spraying in eyes. Contents under pressure. Do not puncture or incinerate. Do not expose to heat or store at temperatures above 120°F/50°C or in enclosed places that could overheat
• Do not use on broken skin. Stop use if rash or irritation occurs.
• Ask a doctor before using if you have kidney disease.
• USE ONLY AS DIRECTED. INTENTIONAL MISUSE BY DELIBERATELY CONCENTRATING AND INHALING THE CONTENTS CAN BE HARMFUL OR FATAL.

Help stop inhalation abuse. For information visit www.inhalant.org

• KEEP OUT OF REACH OF CHILDREN.

Directions

FOR UNDERARM USE ONLY

Inactive ingredients

Butane, Cyclopentasiloxane, Hydrofluorocarbon 152a, Isobutane, PPG-14 Butyl Ether, Disteardimonium Hectorite, Fragrance (Parfum), Propane, BHT, Propylene Carbonate.

Questions?

Call us at 1-800-782-8301